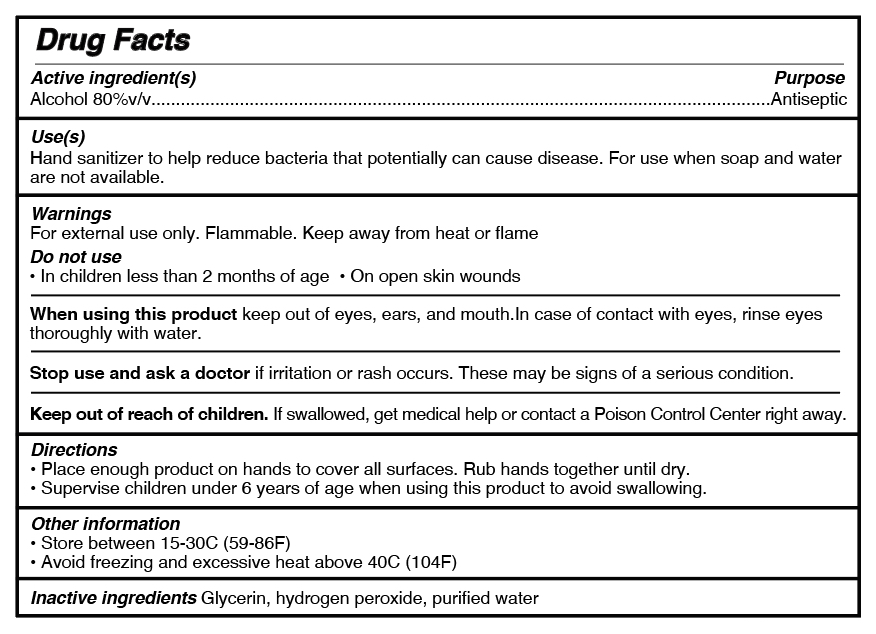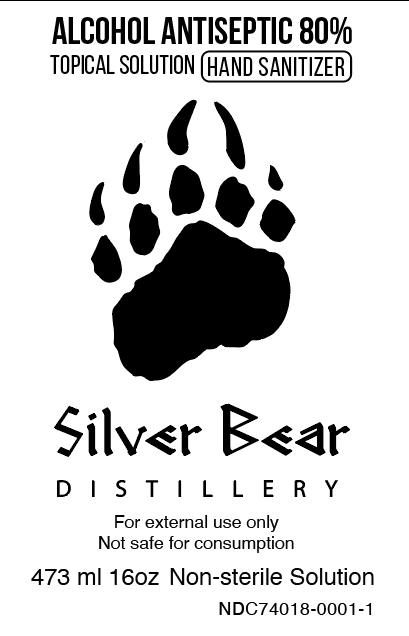 DRUG LABEL: Silver Bear Distillery Hand Sanitizer
NDC: 74018-0001 | Form: LIQUID
Manufacturer: Siver Bear Distillery
Category: otc | Type: HUMAN OTC DRUG LABEL
Date: 20200326

ACTIVE INGREDIENTS: ALCOHOL 141.6 mL/177 mL
INACTIVE INGREDIENTS: GLYCEROL FORMAL 2.57 mL/177 mL; WATER 32.6 mL/177 mL; HYDROGEN PEROXIDE 0.23 mL/177 mL

Active Ingredient & back label

Active Ingredient(s)

Alcohol 80%v/v.....Antiseptic

Use(s) Hand sanitizer to help reduce bacteria that potentially can cause disease. For use when soap aand water are not availeble

Use(s)
Hand sanitizer to help reduce bacteria that potentially can cause disease. For use when soap aand water
are not availeble

Warnings

For external use only. Flammable. Keep away from heat or flame.

Stop Use and and ask a doctor if irritation or rash occurs.These may be signs of a serious condition

Keep Out of reach of children. If swallowed, get medical help or contact Poison Control Center right away.

Directions

Place enough product on hands to cover all surfaces. Rub hands together until dry.

Supervise children under 6 years of age when using this product to avoid swallowing.

Other information

Store between 15-30C (59-86F)

Avoid freezing and excessive heat above 40C (104F)

Inactive ingredients Glycerin, hydrogen peroxide, purified water

DOSAGE AND ADMINISTRATION

TOPICAL SOLUTION

WARNINGS

For external use only

Not safe for consumption

INDICATIONS AND USAGE

TOPICAL SOLUTION hAND SANITIZER

For external use only

PACKAGE LABEL

ALCOHOL ANTICEPTIC 80%

TOPICAL SOLUTION HAND SANITIZER

Silver Bear Distillery

For external use only

Not safe for consumption

473ml 16oz Non-sterile Solution

NDC74018-0001-1